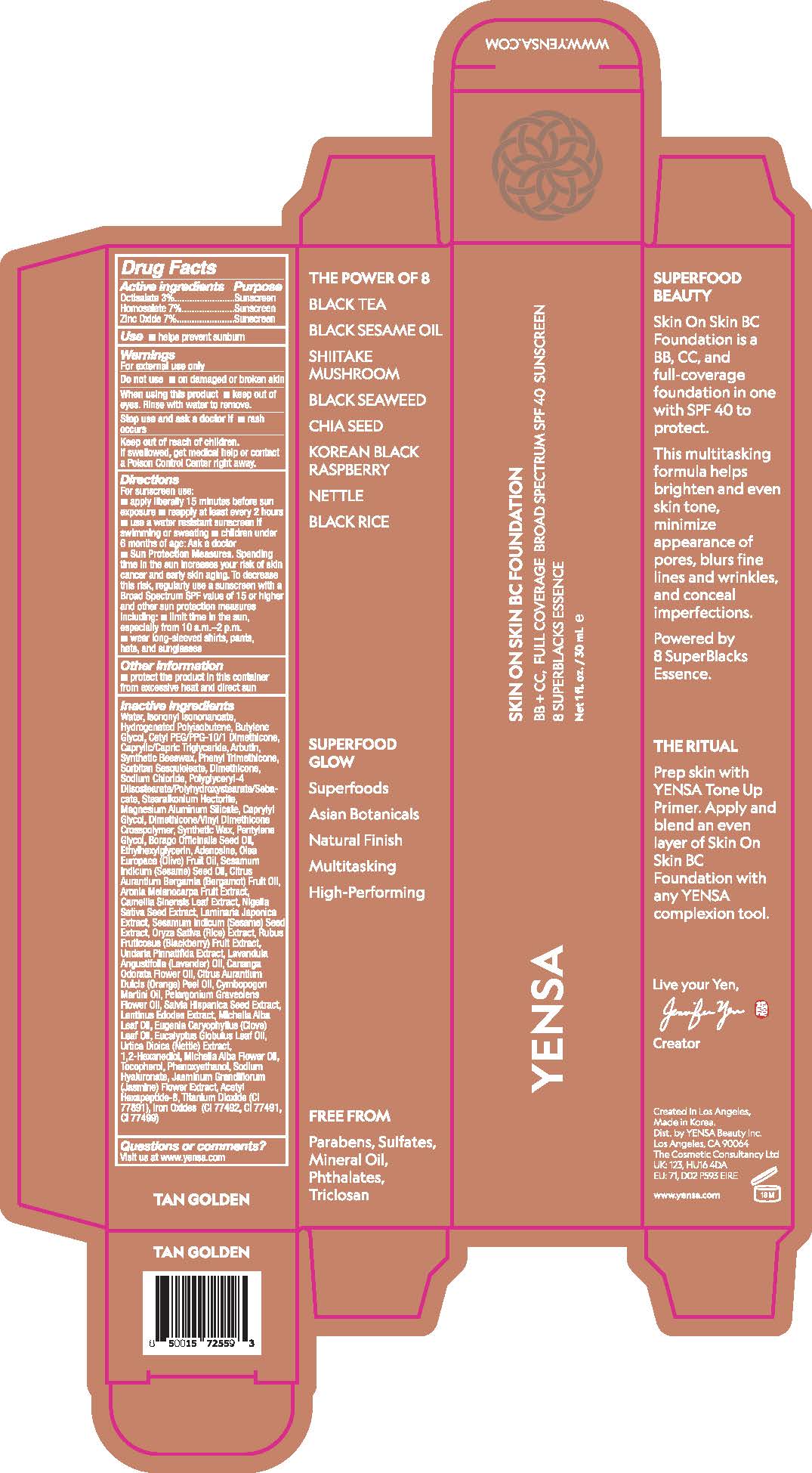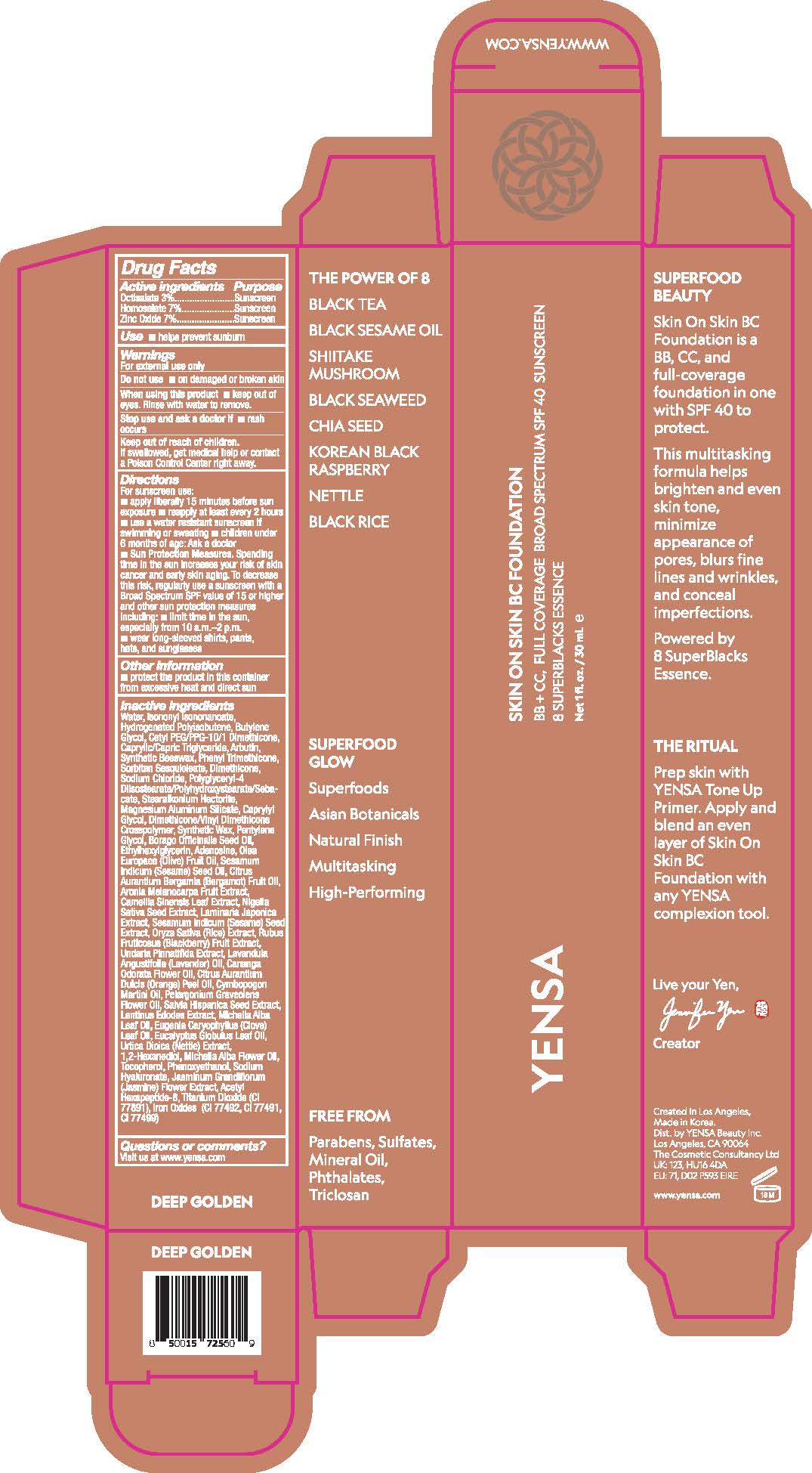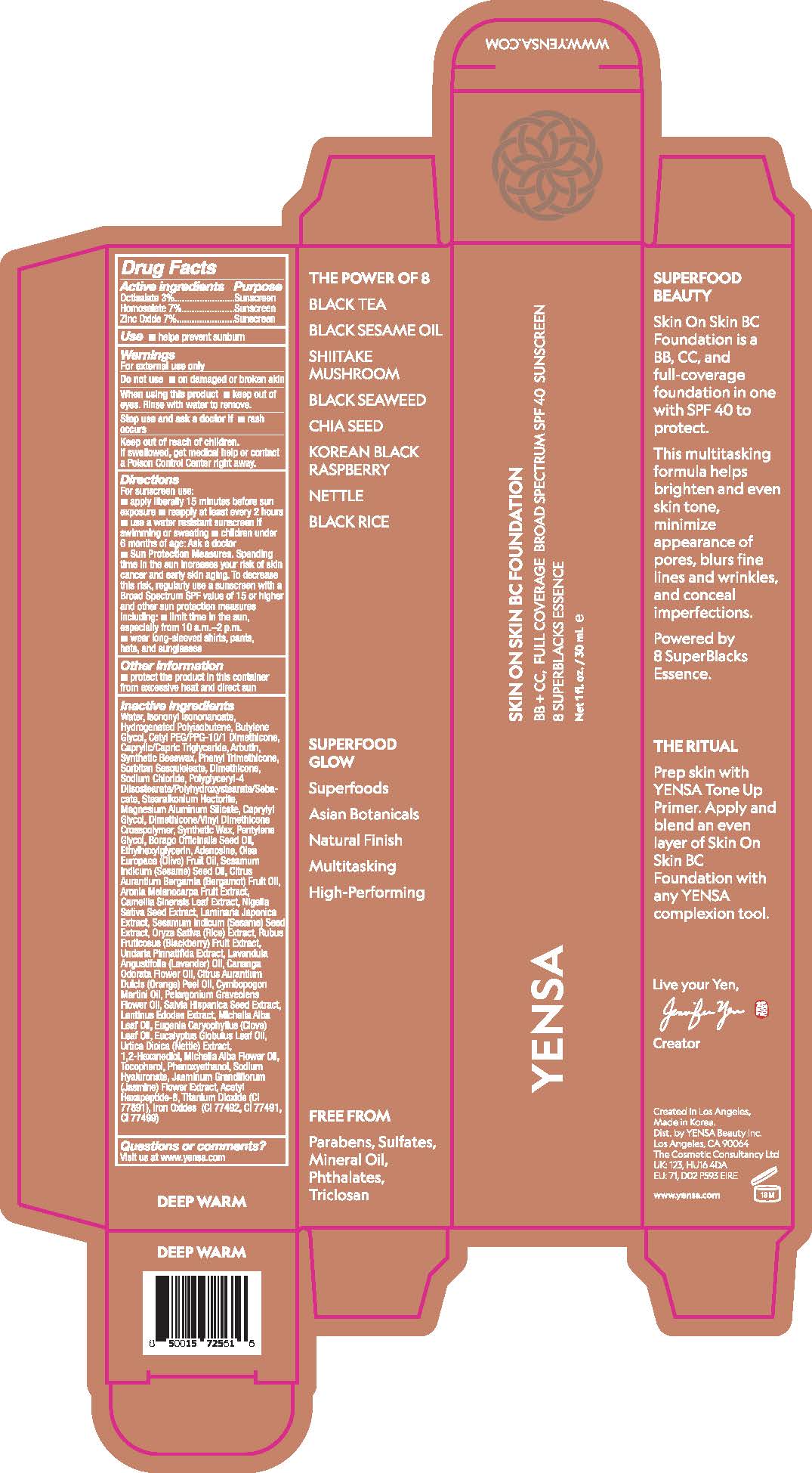 DRUG LABEL: Skin On Skin BC Foundation SPF 40 - Deep Golden
NDC: 72782-117 | Form: CREAM
Manufacturer: YENSA Beauty, LLC
Category: otc | Type: HUMAN OTC DRUG LABEL
Date: 20251218

ACTIVE INGREDIENTS: OCTISALATE 3 g/100 mL; HOMOSALATE 7 g/100 mL; ZINC OXIDE 7 g/100 mL
INACTIVE INGREDIENTS: SESAMUM INDICUM (SESAME) SEED OIL; GREEN TEA LEAF; YLANG-YLANG OIL; BLACKBERRY; BORAGO OFFICINALIS SEED OIL; SODIUM CHLORIDE; PHENOXYETHANOL; ORANGE OIL, COLD PRESSED; POLYGLYCERYL-4 DIISOSTEARATE/POLYHYDROXYSTEARATE/SEBACATE; EUGENIA CARYOPHYLLUS (CLOVE) LEAF OIL; TOCOPHEROL; ISONONYL ISONONANOATE; LAMINARIA JAPONICA; ETHYLHEXYLGLYCERIN; DIMETHICONE; HYALURONATE SODIUM; CETYL PEG/PPG-10/1 DIMETHICONE (HLB 2); SYNTHETIC BEESWAX; 1,2-HEXANEDIOL; ARONIA MELANOCARPA FRUIT JUICE; SESAMUM INDICUM (SESAME) SEED; UNDARIA PINNATIFIDA; LENTINULA EDODES MYCELIUM; MAGNESIUM ALUMINUM SILICATE; PINENE; SORBITAN SESQUIOLEATE; STEARALKONIUM HECTORITE; PHENYL TRIMETHICONE; CHIA SEED; PELARGONIUM GRAVEOLENS FLOWER OIL; FERROUS OXIDE; DIMETHICONE/VINYL DIMETHICONE CROSSPOLYMER (HARD PARTICLE); URTICA DIOICA LEAF; TITANIUM DIOXIDE; WATER; LINALYL ACETATE; RICE GERM; NIGELLA SATIVA SEED; CAPRYLYL GLYCOL; LAVENDER OIL; LINALOOL; LIMONENE, (+)-; BUTYLENE GLYCOL; CAPRYLIC/CAPRIC TRIGLYCERIDE; ARBUTIN; GERANIOL; ACETYL HEXAPEPTIDE-8; SYNTHETIC WAX (1200 MW); HYDROGENATED POLYISOBUTENE (450 MW); BERGAMOT OIL; BETA-CARYOPHYLLENE; ADENOSINE; PENTYLENE GLYCOL

Drug Facts

Active ingredients

Octisalate 3%

Homosalate 7%

Zinc Oxide 7%

Purpose

Sunscreen

Use

- helps prevent sunburn

Warnings

For external use only

Do not use

- on damaged or broken skin

When using this product

- keep out of eyes. Rinse with water to remove.

Stop use and ask a doctor if

- rash occurs

Keep out of reach of children.

If swallowed, get medical help or contact a Poison Control Center right away.

Directions

For sunscreen use:

- apply liberally 15 minutes before sun exposure
- reapply at least every 2 hours
- use a water resistant sunscreen if swimming or sweating
- children under 6 months of age: Ask a doctor
- Sun Protection Measures. Spending time in the sun increases your risk of skin cancer and early skin aging. To decrease this risk, regularly use a sunscreen with a Broad Spectrum SPF value of 15 or higher and other sun protection measures including:
- limit time in the sun, especially from 10 a.m.-2 p.m.
- wear long-sleeved shirts, pants, hats, and sunglasses

Other information

- protect the product in this container from excessive heat and direct sun

Inactive ingredients

Water, Isononyl Isononanoate, Hydrogenated Polyisobutene, Butylene Glycol, Cetyl PEG/PPG-10/1 Dimethicone, Caprylic/Capric Triglyceride, Arbutin, Synthetic Beeswax, Phenyl Trimethicone, Sorbitan Sesquioleate, Dimethicone, Sodium Chloride, Polyglyceryl-4 Diisostearate/Polyhydroxystearate/Sebacate, Stearalkonium Hectorite, Magnesium Aluminum Silicate, Caprylyl Glycol, Dimethicone/Vinyl Dimethicone Crosspolymer, Synthetic Wax, Pentylene Glycol, Borago Officinalis Seed Oil, Ethylhexylglycerin, Adenosine, Olea Europaea (Olive) Fruit Oil, Sesamum Indicum (Sesame) Seed Oil, Citrus Aurantium Bergamia (Bergamot) Fruit Oil, Aronia Melanocarpa Fruit Extract, Camellia Sinensis Leaf Extract, Nigella Sativa Seed Extract, Laminaria Japonica Extract, Sesamum Indicum (Sesame) Seed Extract, Oryza Sativa (Rice) Extract, Rubus Fruticosus (Blackberry) Fruit Extract, Undaria Pinnatifida Extract, Lavandula Angustifolia (Lavender) Oil, Cananga Odorata Flower Oil, Citrus Aurantium Dulcis (Orange) Peel Oil, Cymbopogon Martini Oil, Pelargonium Graveolens Flower Oil, Salvia Hispanica Seed Extract, Lentinus Edodes Extract, Michelia Alba Leaf Oil, Eugenia Caryophyllus (Clove) Leaf Oil, Eucalyptus Globulus Leaf Oil, Urtica Dioica (Nettle) Extract, 1,2-Hexanediol, Michelia Alba Flower Oil, Tocopherol, Phenoxyethanol, Sodium Hyaluronate, Jasminum Grandiflorum (Jasmine) Flower Extract, Acetyl Hexapeptide-8, Titanium Dioxide, Iron Oxides

Questions or comments?

Visit us at www.yensa.com

PRINCIPAL DISPLAY PANEL - 30 ML TUBE LABEL - TAN GOLDEN

YENSA

SKIN ON SKIN BC FOUNDATION

BB + CC, FULL COVERAGE BROAD SPECTRUM SPF 40 SUNSCREEN

8 SUPERBLACKS ESSENCE

Net 1 fl. oz. / 30 mL ℮

PRINCIPAL DISPLAY PANEL - 30 ML TUBE LABEL - DEEP GOLDEN

YENSA

SKIN ON SKIN BC FOUNDATION

BB + CC, FULL COVERAGE BROAD SPECTRUM SPF 40 SUNSCREEN

8 SUPERBLACKS ESSENCE

Net 1 fl. oz. / 30 mL ℮

PRINCIPAL DISPLAY PANEL - 30 ML TUBE LABEL - DEEP WARM

YENSA

SKIN ON SKIN BC FOUNDATION

BB + CC, FULL COVERAGE BROAD SPECTRUM SPF 40 SUNSCREEN

8 SUPERBLACKS ESSENCE

Net 1 fl. oz. / 30 mL ℮